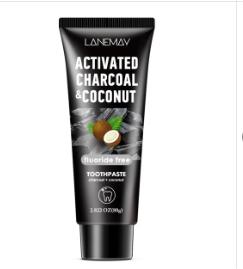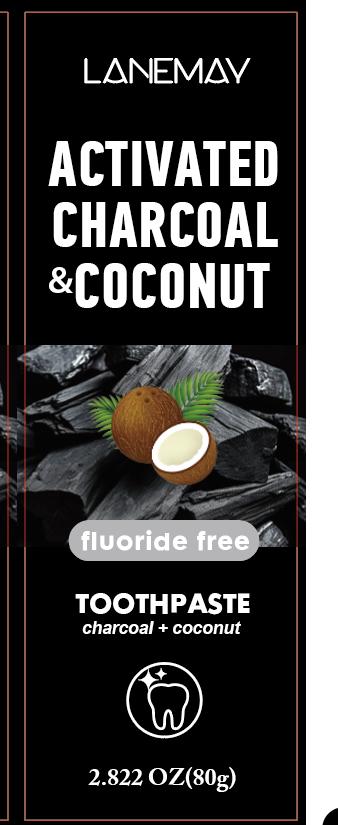 DRUG LABEL: CharcoalCoconutToothpaste
NDC: 84025-059 | Form: GEL, DENTIFRICE
Manufacturer: Guangzhou Yanxi Biotechnology Co., Ltd
Category: otc | Type: HUMAN OTC DRUG LABEL
Date: 20240710

ACTIVE INGREDIENTS: HYDRATED SILICA 3 mg/80 g; ALUMINUM HYDROXIDE 2 mg/80 g
INACTIVE INGREDIENTS: WATER

DOSAGE AND ADMINISTRATION

use as a normal tooth cream

WARNINGS

Keep out of Children

INACTIVE INGREDIENT

Aqua

INDICATIONS AND USAGE

For daily tooth care

Keep out of Children

PURPOSE

lt makes teeth whiter.